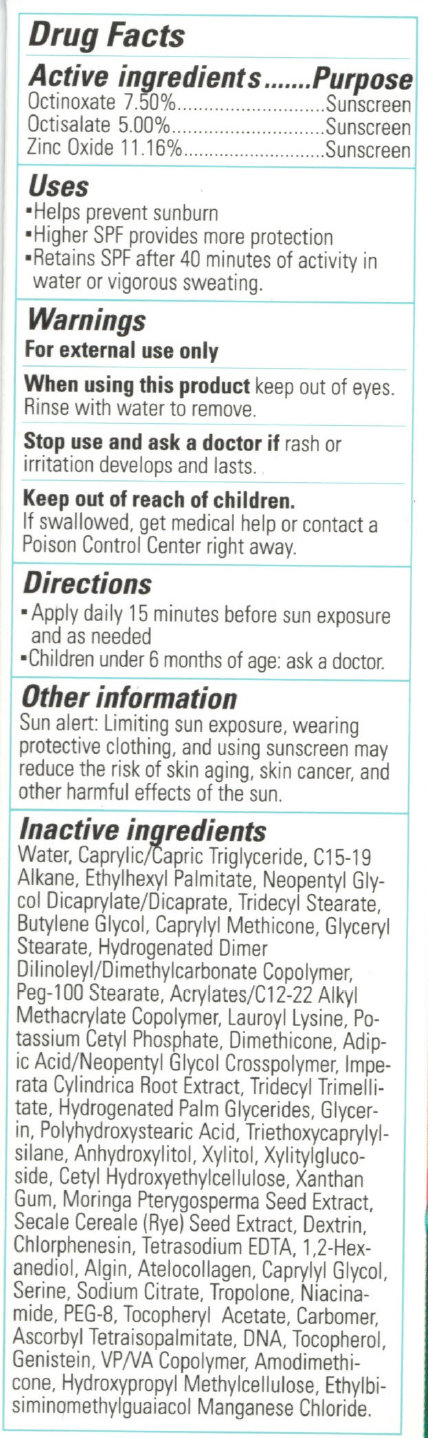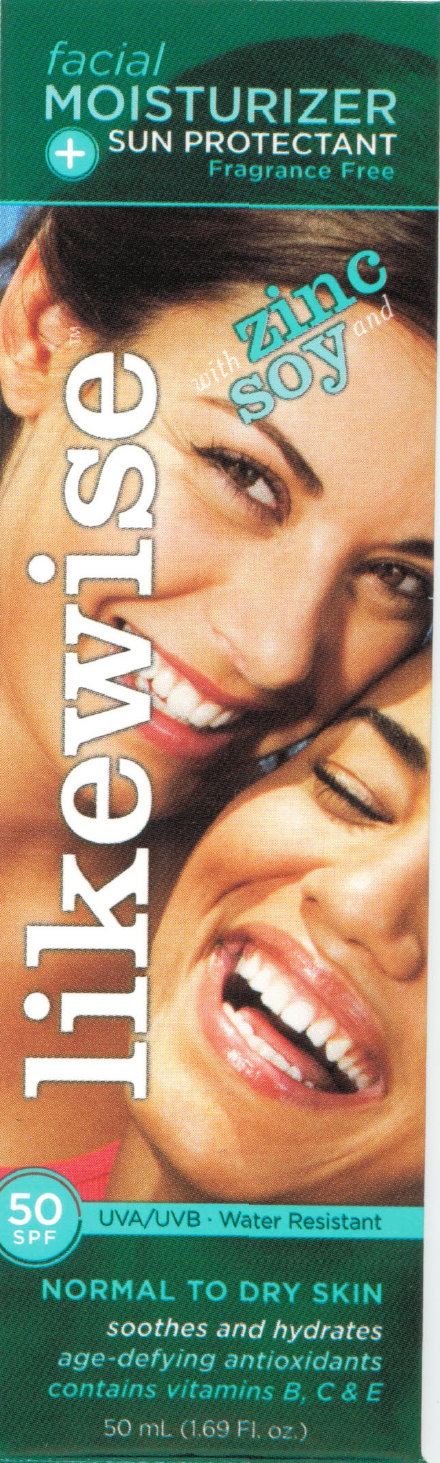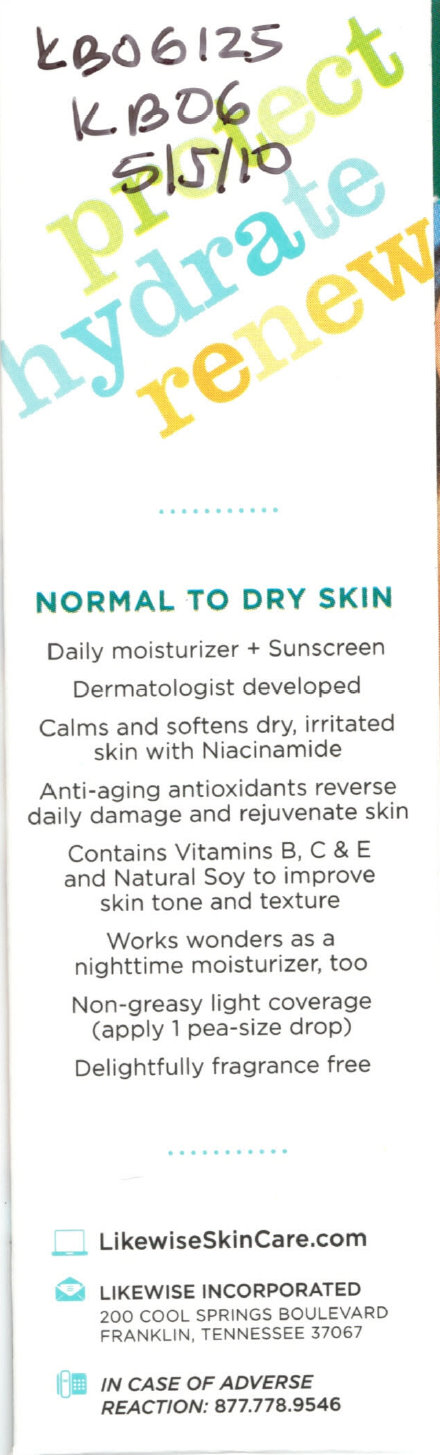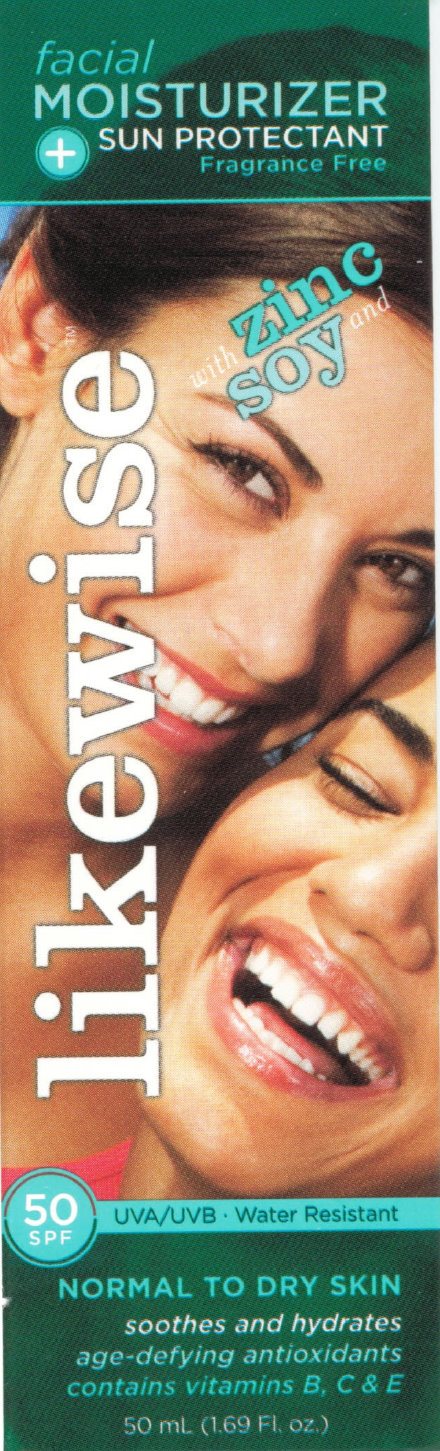 DRUG LABEL: Likewise Facial Moisturizer - Sun Protectant SPF 50 Normal to Dry Skin
NDC: 76229-456 | Form: CREAM
Manufacturer: Likewise Incorporated
Category: otc | Type: HUMAN OTC DRUG LABEL
Date: 20231212

ACTIVE INGREDIENTS: OCTINOXATE 75 mg/1 mL; OCTISALATE 50 mg/1 mL; ZINC OXIDE 111.6 mg/1 mL
INACTIVE INGREDIENTS: WATER; MEDIUM-CHAIN TRIGLYCERIDES; ETHYLHEXYL PALMITATE; NEOPENTYL GLYCOL DICAPRATE; TRIDECYL STEARATE; BUTYLENE GLYCOL; GLYCERYL MONOSTEARATE; PEG-100 STEARATE; LAUROYL LYSINE; POTASSIUM CETYL PHOSPHATE; DIMETHICONE; ADIPIC ACID; IMPERATA CYLINDRICA ROOT; TRIDECYL TRIMELLITATE; HYDROGENATED PALM GLYCERIDES; GLYCERIN; TRIETHOXYCAPRYLYLSILANE; ANHYDROXYLITOL; XYLITOL; XYLITYLGLUCOSIDE; XANTHAN GUM; MORINGA OLEIFERA SEED; RYE; ICODEXTRIN; CHLORPHENESIN; EDETATE SODIUM; 1,2-HEXANEDIOL; SODIUM ALGINATE; CAPRYLYL GLYCOL; SERINE; SODIUM CITRATE; TROPOLONE; NIACINAMIDE; POLYETHYLENE GLYCOL 400; HERRING SPERM DNA; TOCOPHEROL; GENISTEIN

Likewise Moisturizer - Sun Protectant SPF 50 Normal to Dry Skin

ACTIVE INGREDIENT

Active Ingredients..............Purpose Octinoxate 7.50%............Sunscreen Octisalate 5.00%.............Sunscreen Zinc Oxide 11.16%..........Sunscreen

PURPOSE

Uses - Helps prevent sunburn - Higher SPF provides more protection - Retains SPF after 40 minutes of activity in water or vigorous sweating.

Warnings For external use only

When using this product keep out of eyes. Rinse with water to remove.

Stop use and ask a doctor if rash or irritation develops and lasts.

Keep out of reach of children.

If swallowed, get medical help or contact a Poison Control Center right away.

OTHER SAFETY INFORMATION

If swallowed, get medical help or contact a Poison Control Center right away.

DOSAGE AND ADMINISTRATION

Directions - Apply daily 15 minutes before sun exposure and as needed - Children under 6 months of age: ask a doctor.

Other information Sun alert: Limiting sun exposure, wearing protective clothing, and using sunscreen may reduce the risk of skin aging, skin cancer, and other harmful effects of the sun.

INACTIVE INGREDIENT

Inactive ingredients Water, Caprylic/Capric Triglyceride, C15-19 Alkane, Ethylhexyl Palmitate, Neopentyl Glycol Dicaprylate/Dicaprate, Tridecyl Stearate, Butylene Glycol, Caprylyl Methicone, Glyceryl Stearate, Hydrogenated Dimer Dilinoleyl/Dimethylcarbonate Copolymer, Peg-100 Stearate, Acrylated/C-12-22 Alkyl Methacrylate Copolymer, Lauroyl Lysine, Potassium Cetyl Phosphate, Dimethicone, Adipic Acid/Neopentyl Glycol Crosspolymer, Imperata Cylindrica Root Extract, Tridecyl Trimellitate, Hydrogenated Palm Glycerides, Glycerin, Polyhydroxystearic Acid, Triethoxycaprylylsilane, Anhydroxylitol, Xylitol, Xylitylglucoside, Cetyl Hydroxyethylcellulose, Xanthan Gum, Moringa Pterygosperma Seed Extract, Secale Cereale (Rye) Seed Extract, Dextrin, Chlorphenesin, Tetrasodium EDTA, 1,2-Hexanediol, Algin, Atelocollagen, Caprylyl Glycol, Serine, Sodium Citrate, Tropolone, Niacinamide, PEG-8, Tocopheryl Acetate, Carbomer, Ascorbyl Tetraisopalmitate, DNA, Tocopherol, Genistein, VP/VA Copolymer, Amodimethicone, Hydroxypropyl Methylcellulose, Ethylbisiminomethylguaiacol Manganese Chloride.

DESCRIPTION

protect hydrate renew . . . . . . . NORMAL TO DRY SKIN Daily moisturizer + Sunscreen Dermatologist developed Calms and softens dry, irritated skin with Niacinamide Anti-aging antioxidants reverse daily damage and rejuvenate skin Contains Vitamins B, C and E and Natural Soy to improve skin tone and texture Works wonders as a nighttime moisturizer, too Non-greasy light coverage (apply 1 pea-size drop) Delightfully fragrance free . . . . . . . LikewiseSkinCare.com LIKEWISE INCORPORATED 200 COOL SPRINGS BOULEVARD FRANKLIN, TENNESSEE 37067 IN CASE OF ADVERSE REACTION: 877.778.9546

Uses

- Helps prevent sunburn
- Higher SPF provides more protection
- Retains SPF after 40 minutes of activity in water or vigorous sweating.

Drug Facts

PACKAGE LABEL

facial MOISTURIZER + SUN PROTECTANT Fragrance Free likewise with Zinc Soy and 50 SPF UVA/UVB - Water Resistant NORMAL TO DRY SKIN soothes and hydrates age-defying antioxidants contains vitamins B, C and E 50 mL (1.69 Fl.oz.)

PACKAGE LABEL

protect hydrate renew LikewiseSkinCare.com LIKEWISE INCORPORATED 200 COOL SPRINGS BOULEVARD FRANKLIN, TENNESSEE 37067 IN CASE OF ADVERSE REACTION: 877.778.9546